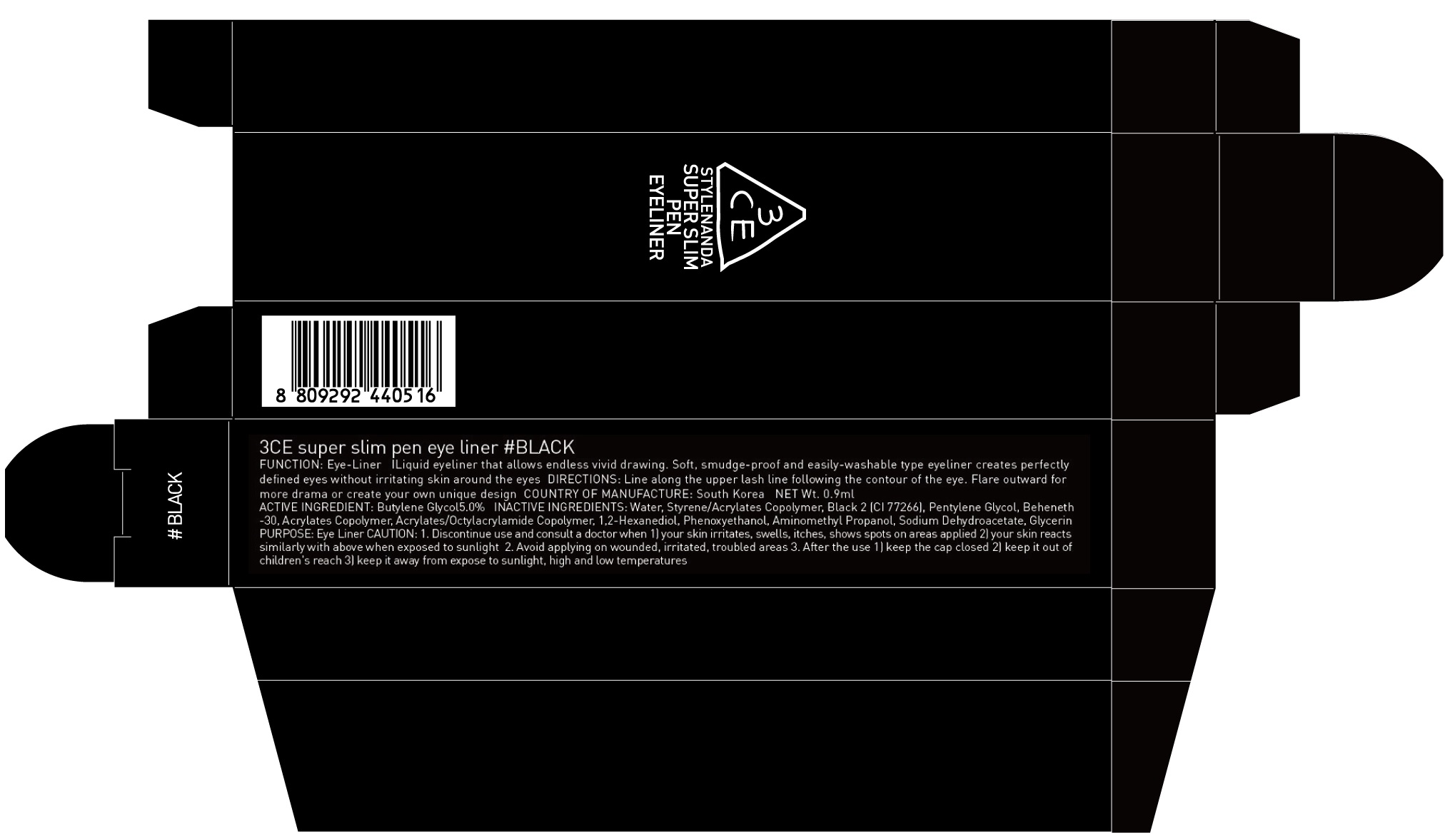 DRUG LABEL: 3CE SUPER SLIM PEN EYE LINER BLACK
NDC: 60764-017 | Form: LIQUID
Manufacturer: Nanda Co., Ltd
Category: otc | Type: HUMAN OTC DRUG LABEL
Date: 20160921

ACTIVE INGREDIENTS: Butylene Glycol 0.04 g/0.9 mL
INACTIVE INGREDIENTS: Water; Pentylene Glycol

ACTIVE INGREDIENT

Active Ingredient: Butylene Glycol 5.0%

INACTIVE INGREDIENT

Inactive Ingredients: Water, Styrene/Acrylates Copolymer, Black 2 (CI 77266), Pentylene Glycol, Beheneth-30, Acrylates Copolymer, Acrylates/Octylacrylamide Copolymer, 1,2-Hexanediol, Phenoxyethanol, Aminomethyl Propanol, Sodium Dehydroacetate, Glycerin

CAUTION

CAUTION: 1. Discontinue use and consult a doctor when - your skin irritates, swells, itches, shows spots on areas applied - your skin reacts similarly with above when exposed to sunlight 2. Avoid applying on wounded, irritated, troubled areas 3. After the use - keep the cap closed - keep it out of children's reach - keep it away from expose to sunlight, high and low temperatures

PURPOSE

Purpose: Eye Liner

KEEP OUT OF REACH OF CHILDREN

keep it out of children's reach

INSTRUCTIONS

INSTRUCTIONS: Liquid eyeliner that allows endless vivid drawing. Soft, smudge-proof and easily-washable type eyeliner creates perfectly defined eyes without irritating skin around the eyes

Directions

Directions: Line along the upper lash line following the contour of the eye. Flare outward for more drama or create your own unique design.